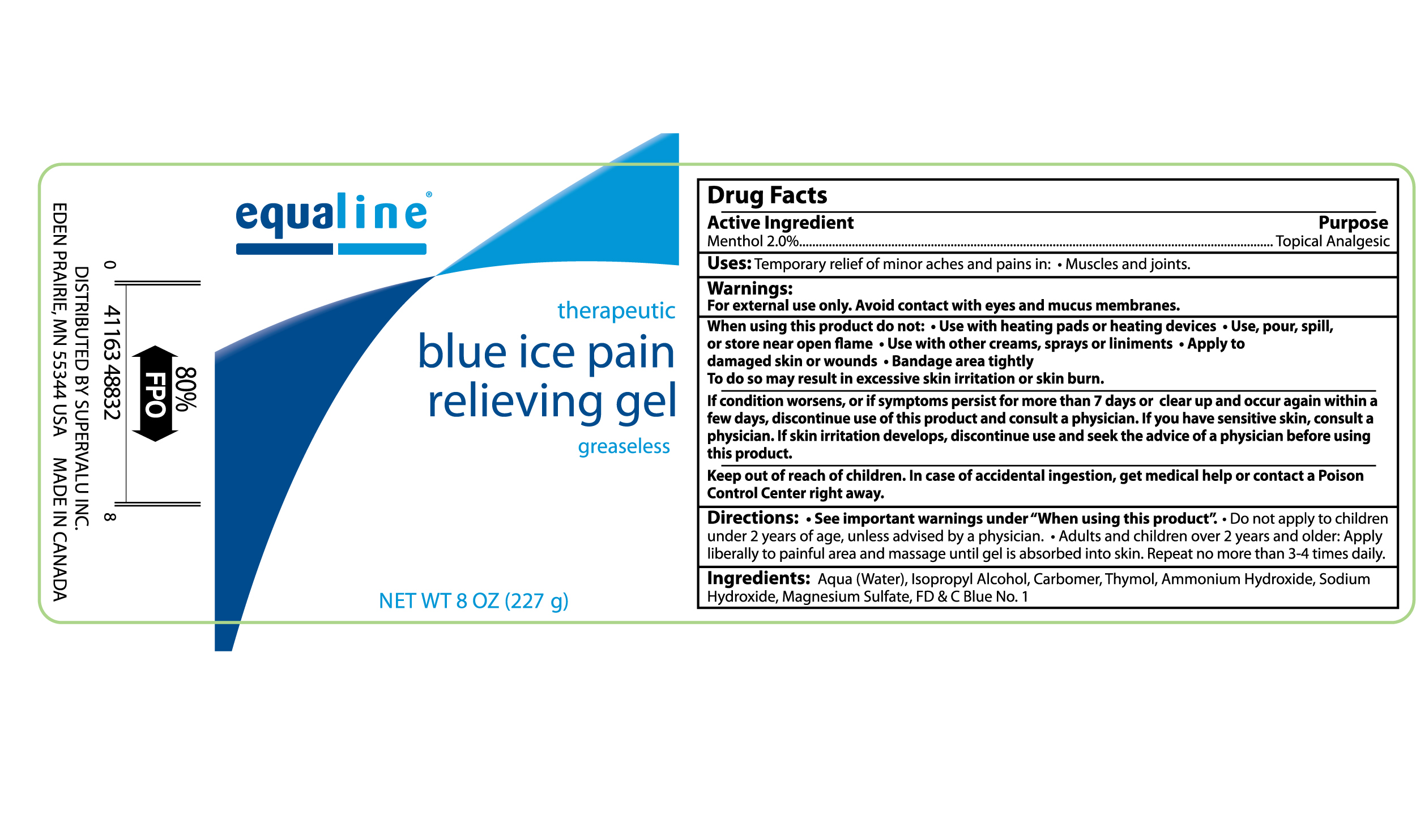 DRUG LABEL: EQUALINE BLUE ICE PAIN RELIEVING
NDC: 41163-488 | Form: GEL
Manufacturer: SUPERVALU INC
Category: otc | Type: HUMAN OTC DRUG LABEL
Date: 20111003

ACTIVE INGREDIENTS: MENTHOL 2 g/100 g
INACTIVE INGREDIENTS: WATER; ISOPROPYL ALCOHOL; THYMOL; AMMONIA; SODIUM HYDROXIDE; MAGNESIUM SULFATE, UNSPECIFIED

Drug Facts

Active Ingredient Purpose

Menthol 2.0% ..........................................................................Topical Analgesic

PURPOSE

Uses: Temporary relief of minor aches and pains in: Muscles and joints.

Warnings:

For external use only. Avoid contact with eyes and mucus membranes.

When using this product do not:

- Use with heating pads or heating devices
- Use, pour, spill, or store near open flame
- Use with other creams, sprays or liniments
- Apply to damaged skin or wounds
- Bandage area tightly

To do so may result in excessive skin irritation or skin burn.

STOP USE

If condition worsens, or if symptoms persist for more than 7 days or clear up and occur again within a few days, discontinue use of this product

and consult a physician. If you have sensitive skin, consult a physician. If skin irritation develops, discontinue use and seek the advice of a physician before

using this product.

Keep out of reach of children. In case of accidental ingestion, get medical help or contact a Poison Control Center right away.

Directions:

- See important warnings under "When using this product."
- Do not apply to children under 2 years of age, unless advised by a physician
- Adults and children over 2 years and older: Apply liberally to painful area and massage until gel is absorbed into skin. Repeat no more than 3-4 times daily

INACTIVE INGREDIENT

Inactive Ingredients: Aqua (water), Isopropyl Alcohol, Carbomer, Thymol, Ammonium Hydroxide, Sodium Hydroxide, Magnesium Sulfate, FD and C Blue No.1

DOSAGE AND ADMINISTRATION

DISTRIBUTED BY SUPERVALU INC.

EDEN PRAIRIE, MN 55344 USA

MADE IN CANADA

PACKAGE LABEL

Enter section text here